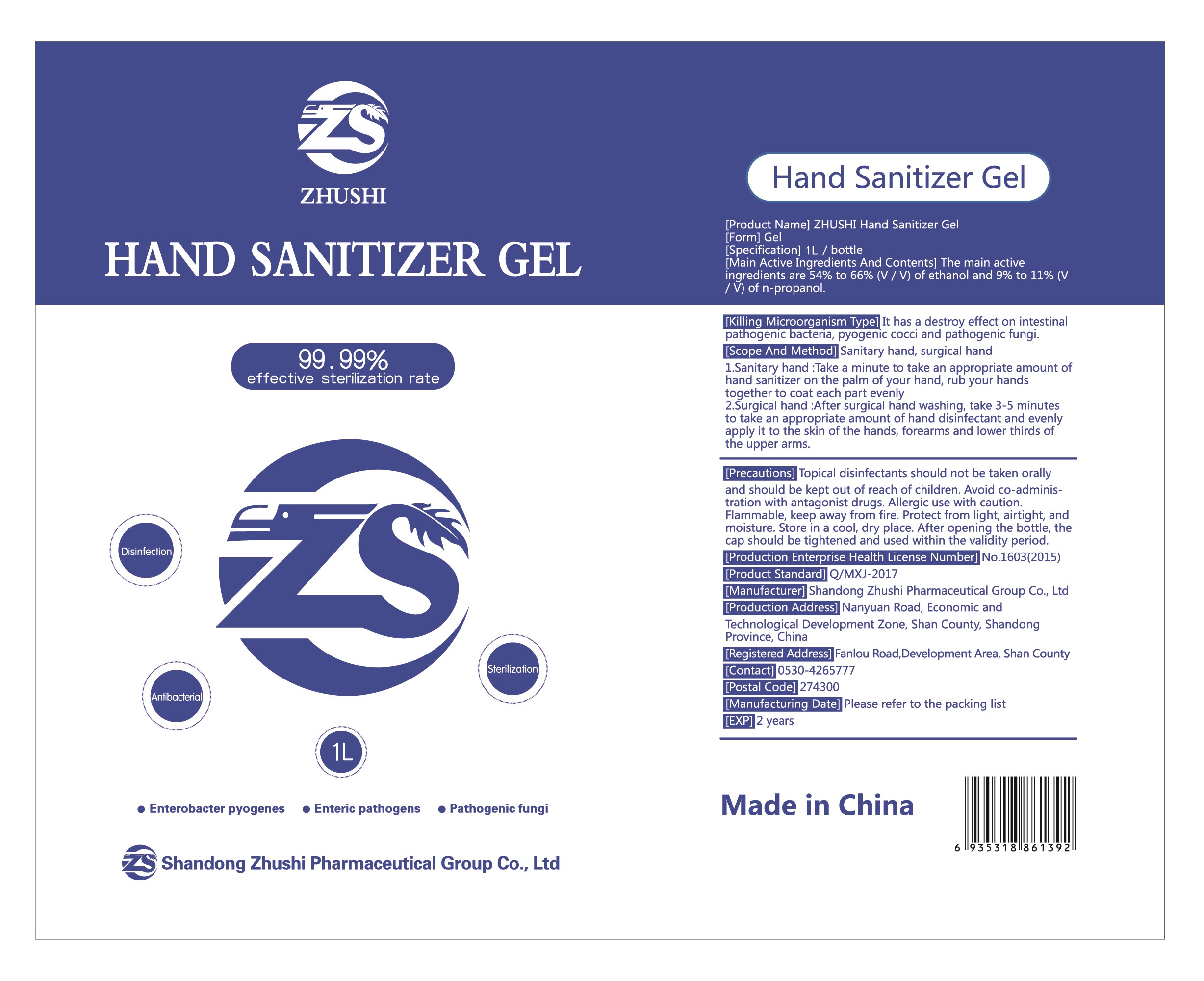 DRUG LABEL: Aoliben ZHUSHI hand sanitizer gel
NDC: 56040-007 | Form: GEL
Manufacturer: Shandong Zhushi Pharmaceutical Group Co., Ltd
Category: otc | Type: HUMAN OTC DRUG LABEL
Date: 20220310

ACTIVE INGREDIENTS: ALCOHOL 640 mL/1000 mL; PROPYL ALCOHOL 80.36 g/1000 mL
INACTIVE INGREDIENTS: TROLAMINE; WATER; POLYACRYLIC ACID (250000 MW)

DOSAGE AND ADMINISTRATION

Protect from light, airtight, and moisture. Store in a cool, dry place.

INACTIVE INGREDIENT

Carbomer 980

Triethanolamine

Purified water

INDICATIONS AND USAGE

1.Sanitary hand :Take a minute to take an appropriate amount of hand sanitizer on the palm of your hand, rub your hands together to coat each part evenly
2.Surgical hand :After surgical hand washing, take 3-5 minutes to take an appropriate amount of hand disinfectant and evenly apply it to the skin of the hands, forearms and lower thirds of the upper arms.

ACTIVE INGREDIENT

Alcohol

N-propanol

KEEP OUT OF REACH OF CHILDREN

Topical disinfectants should not be taken orally and should be kept out of reach of children.

PURPOSE

Disinfection
Sterilization

WARNINGS

Flammable, keep away from fire.